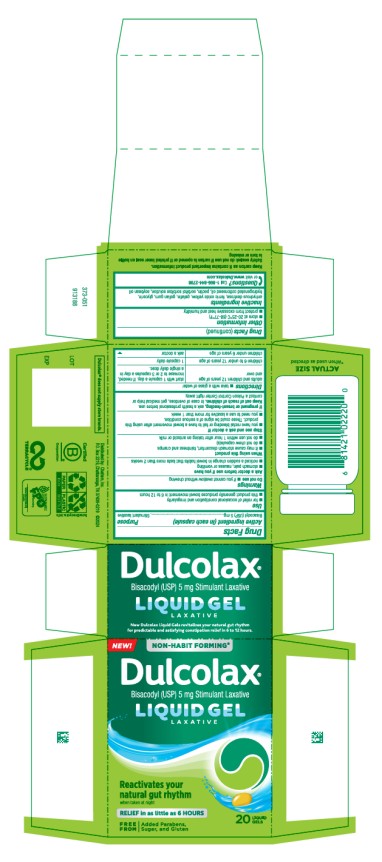 DRUG LABEL: Dulcolax Laxative
NDC: 41167-0222 | Form: CAPSULE, LIQUID FILLED
Manufacturer: Chattem, Inc.
Category: otc | Type: HUMAN OTC DRUG LABEL
Date: 20260226

ACTIVE INGREDIENTS: BISACODYL 5 mg/1 1
INACTIVE INGREDIENTS: ANHYDROUS DEXTROSE; FERRIC OXIDE YELLOW; GELATIN; GELLAN GUM; GLYCERIN; HYDROGENATED COTTONSEED OIL; PECTIN; SORBITOL SOLUTION; SOYBEAN OIL

Dulcolax Liquid Gel Laxative

Drug Facts

Active ingredient (in each capsule)

Bisacodyl (USP) 5 mg

Purpose

Stimulant laxative

Use

■ for relief of occasional constipation and irregularity

■ this product generally produces bowel movement in 6 to 12 hours

Warnings

Do not use ■ if you cannot swallow without chewing

Ask a doctor before use if you have

■ stomach pain, nausea or vomiting

■ noticed a sudden change in bowel habits that lasts more than 2 weeks

When using this product

■ it may cause stomach discomfort, faintness and cramps

■ do not chew capsule(s)

■ do not use within 1 hour after taking an antacid or milk

Stop use and ask a doctor if

■ you have rectal bleeding or fail to have a bowel movement after using this product. These could be signs of a serious condition.

■ you need to use a laxative for more than 1 week

If pregnant or breast-feeding,

ask a health professional before use.

Keep out of reach of children.

In case of overdose, get medical help or contact a Poison Control Center right away.

Directions

■ take with a glass of water

adults and children 12 years of age and over start with 1 capsule a day. If needed, increase to 2 or 3 capsules a day in a single daily dose.

children 6 to under 12 years of age 1 capsule daily

children under 6 years of age ask a doctor

Other information

■ store at 20-25°C (68-77°F)

■ protect from excessive heat and humidity

Inactive ingredients

anhydrous dextrose, ferric oxide yellow, gelatin, gellan gum, glycerin, hydrogenated cottonseed oil, pectin, sorbitol sorbitan solution, soybean oil

Questions?

Call 1-866-844-2798 or visit www.Dulcolax.com

Keep carton as it contains important product information.

Principal Display Panel

Dulcolax
Bisacodyl (USP) 5 mg Stimulant Laxative
LIQUID GEL
LAXATIVE
20 LIQUID GELS